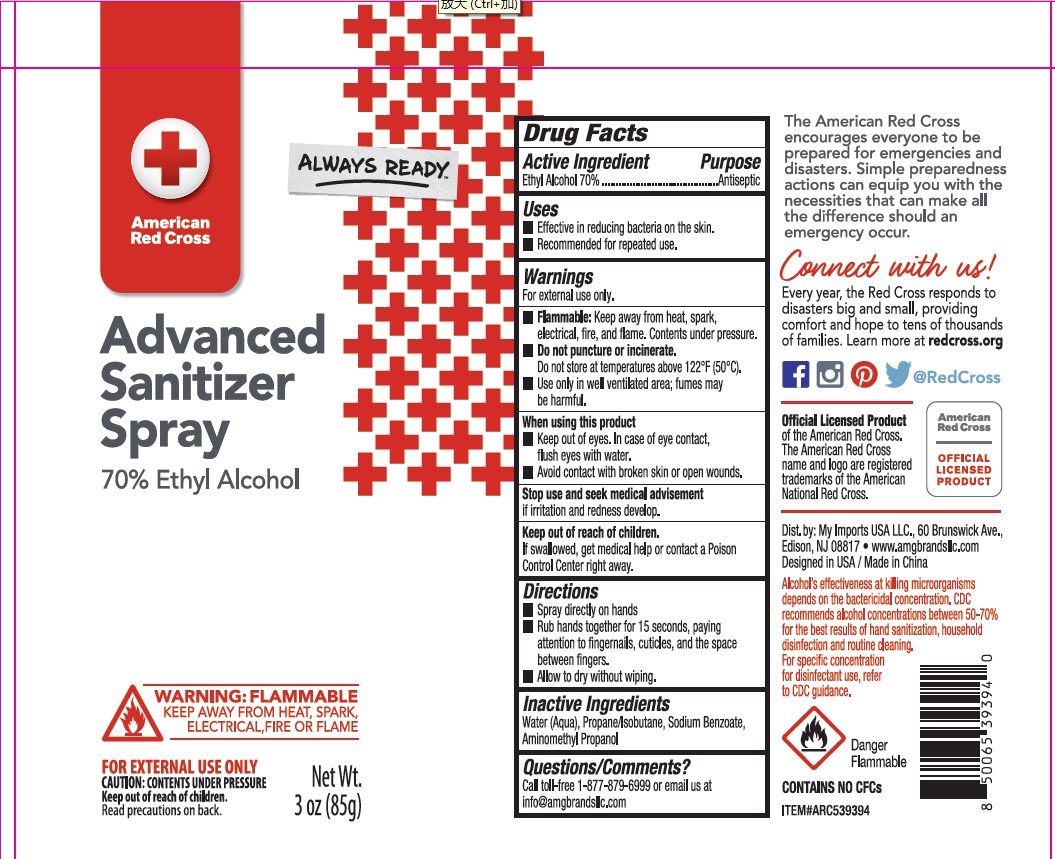 DRUG LABEL: AMERICAN RED CROSS ADVANCED SANITIZER ETHYL ALCOHOL
NDC: 75742-038 | Form: AEROSOL, SPRAY
Manufacturer: Zhejiang Guoyao Jingyue Aerosol Co., Ltd.
Category: otc | Type: HUMAN OTC DRUG LABEL
Date: 20241225

ACTIVE INGREDIENTS: ALCOHOL 70 mL/100 g
INACTIVE INGREDIENTS: WATER; PROPANE; ISOBUTANE; SODIUM BENZOATE; AMINOMETHYLPROPANOL

AMERICAN RED CROSS ADVANCED SANITIZER SPRAY 70% ETHYL ALCOHOL

Active ingredient

Ethyl Alcohol 70%

Purpose

Antiseptic

Uses

- effective in reducing bacteria on the skin.
- recommended for repeated use.

Warnings

For external use only.

- Flammable: keep away from heat, spark, electrical, fire, and flame. Contents under pressure.
- Do not puncture or incinerate. Do not store at temperatures above 122F (50C).
- Use only in well ventilated area; fumes may be harmful.

When using this product

- Keep out of eyes. In case of eye contact, flush eyes with water.
- Avoid contact with broken skin or open wounds.

Stop use and seek medical advisement

If irritation and redness develop.

Keep out of reach of children

If swallowed, get medical help or contact a Poison Control Center right away.

Directions

- Spray directly on hands.
- Rub hands together for 15 seconds, paying attention to fingernails, cuticles, and the space between fingers.
- Allow to dry without wiping.

Inactive ingredients

Water(Auqa)

Propane/Isobutane

Sodium Benzoate

Aminomethyl propanol